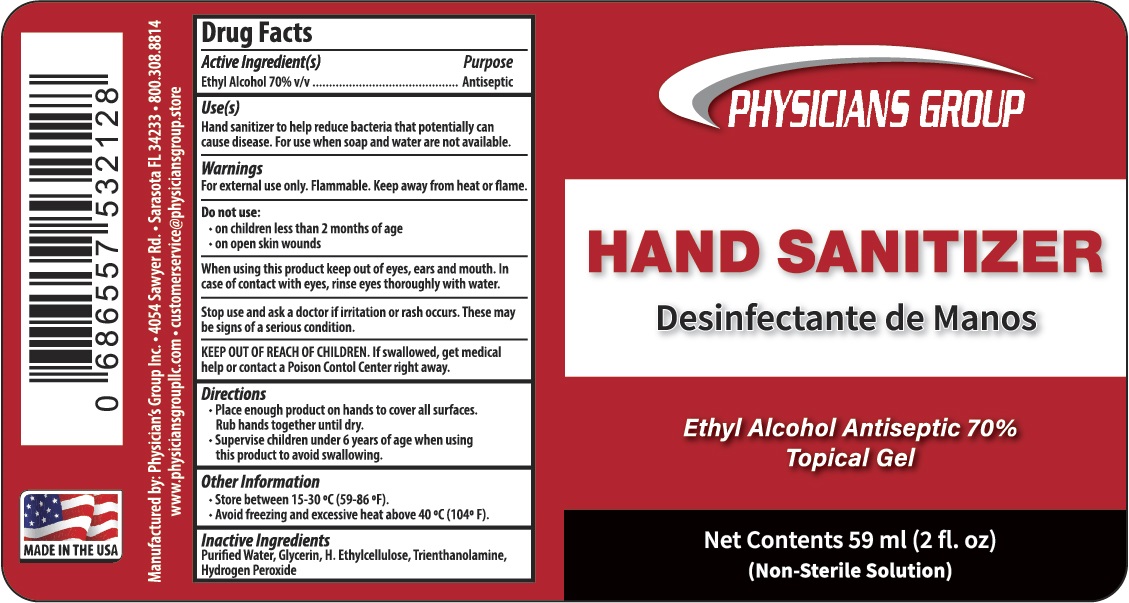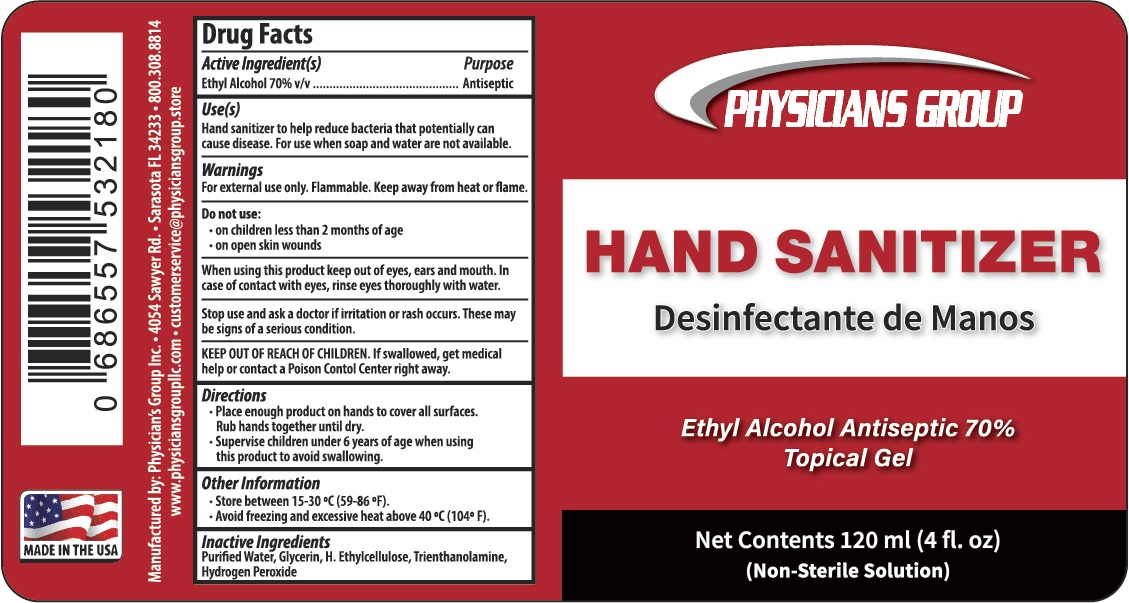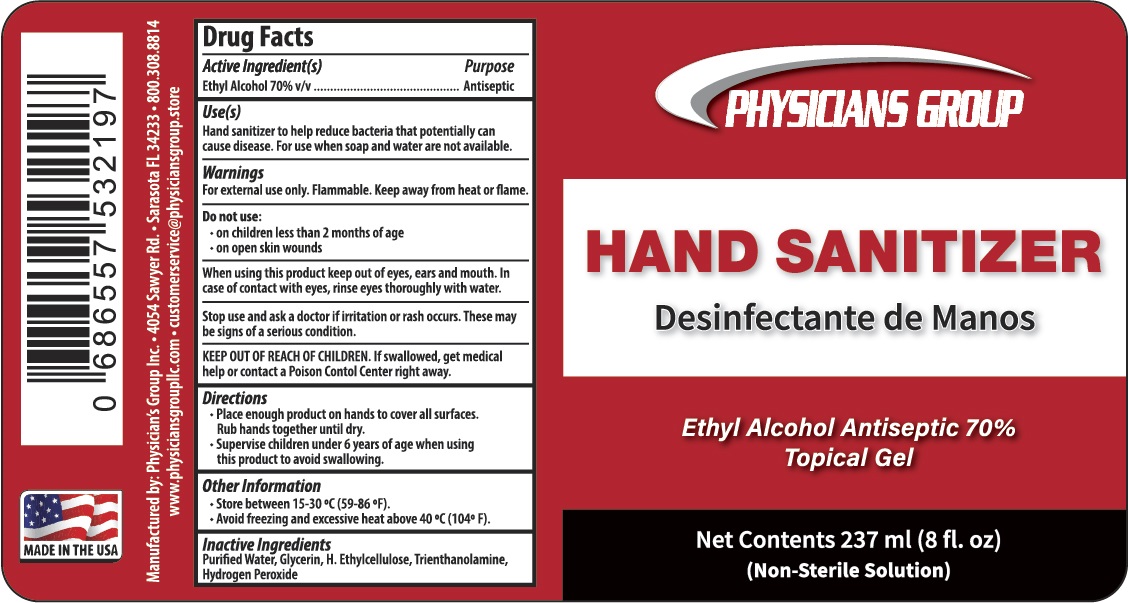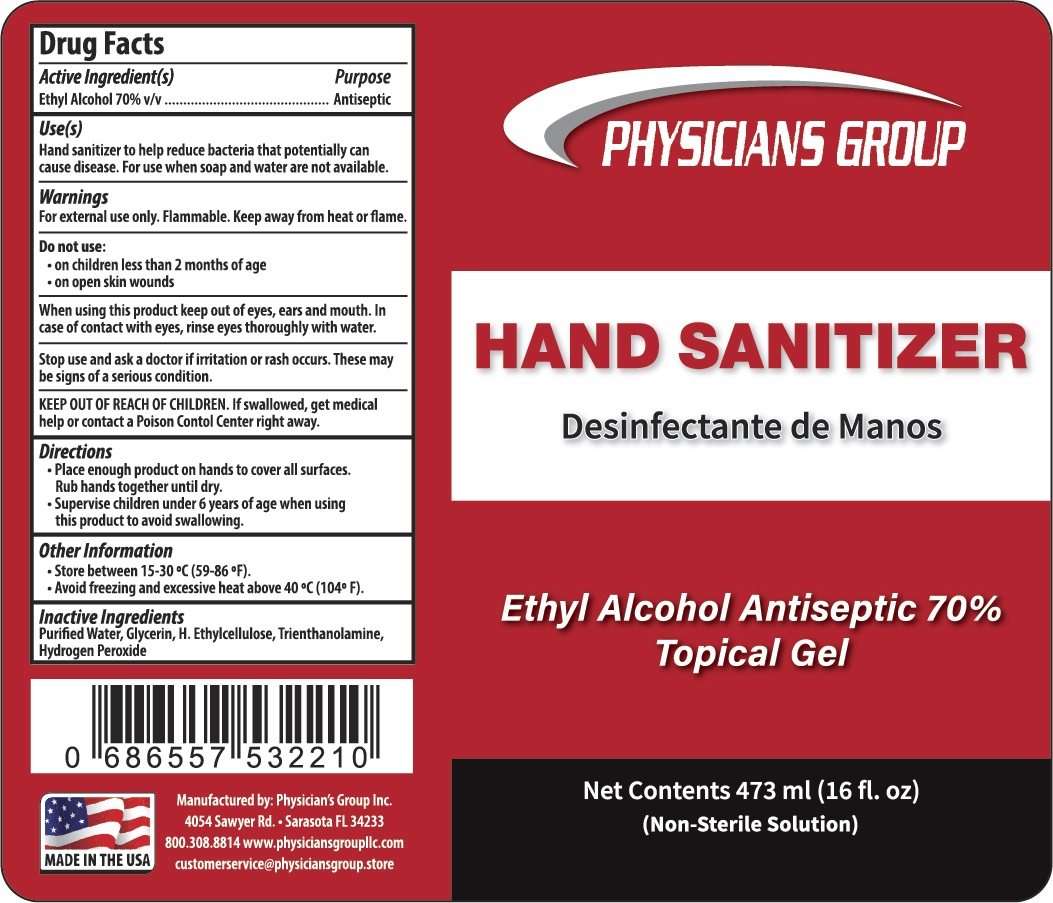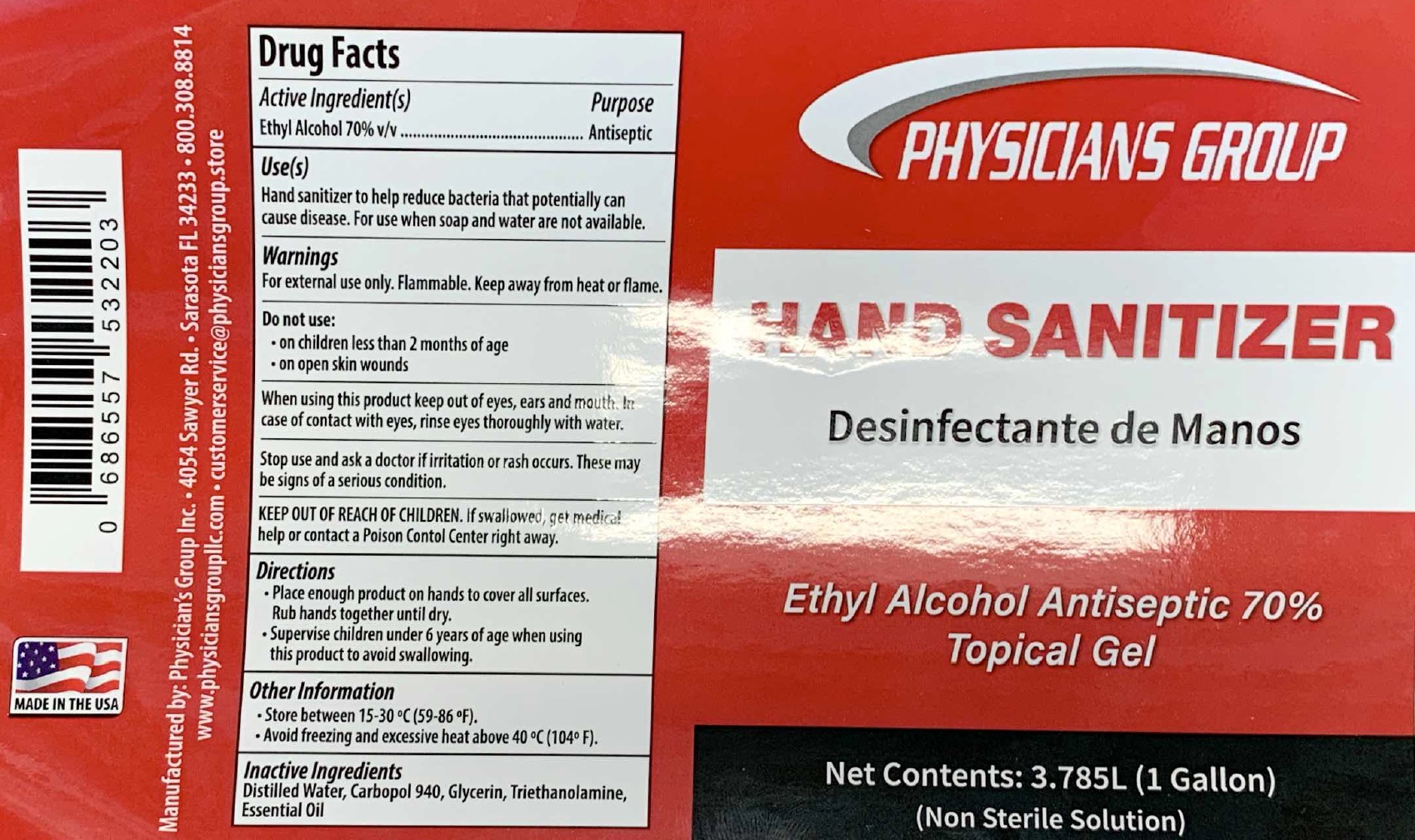 DRUG LABEL: Physicians Group Hand Sanitizer Gel
NDC: 77808-002 | Form: GEL
Manufacturer: Physicians Group LLC
Category: otc | Type: HUMAN OTC DRUG LABEL
Date: 20231226

ACTIVE INGREDIENTS: ALCOHOL 0.7 mL/1 mL
INACTIVE INGREDIENTS: WATER; GLYCERIN; ETHYLCELLULOSE, UNSPECIFIED; TROLAMINE; HYDROGEN PEROXIDE

Physicians Group Hand Sanitizer Gel

Active Ingredient(s)

Ethyl Alcohol 70% v/v

Purpose

Antiseptic

Use(s)

Hand sanitizer to help reduce bacteria that potentially can cause disease. For use when soap and water are not available.

Warnings

For external use only. Flammable. Keep away from heat or flame.

Do not use:

- on children less than 2 months of age
- on open skin wounds

When using this product

keep out of eyes, ear and mouth. In case of contact with eyes, rinse eyes thoroughly with water.

Stop use and ask a doctor

if irritation or rash occurs. These may be signs of a serious condition.

KEEP OUT OF REACH OF CHILDREN

If swallowed, get medical help contact a Poison Control Center right away.

Directions

- Place enough produt on hands to cover all surfaces. Rub hands together until dry.
- Supervise children under 6 years of age when using this product to avoid swallowing.

Other Information

- Store between 15-30 °C (59-86 °F).
- Avoid freezing and excessive heat above 40 °C (104° F).

Inactive Ingredients

Purified Water, Glycerin, H.Ethylcellulose, Trienthanolamine, Hydrogen Peroxide